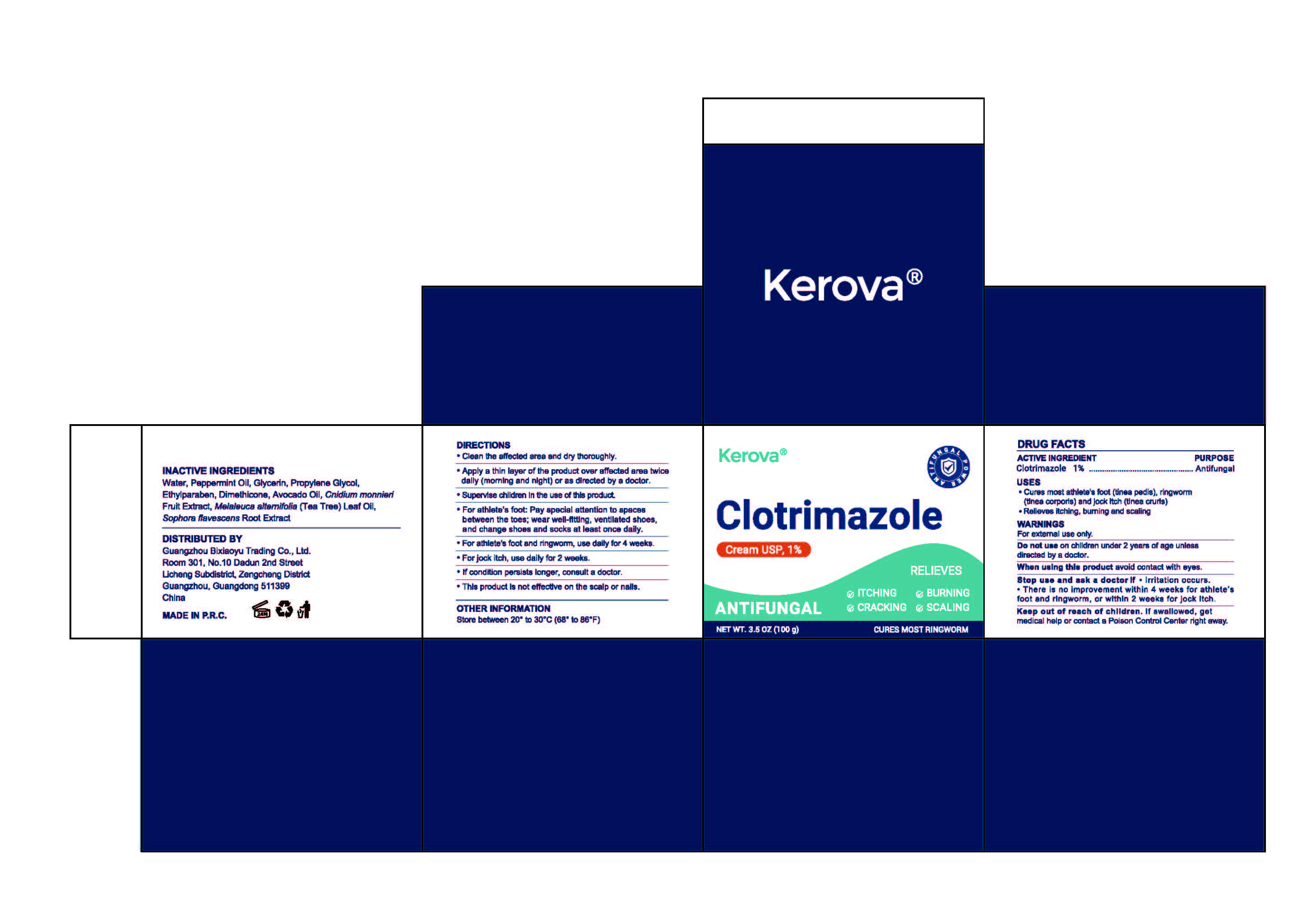 DRUG LABEL: Kerova Clotrimazole
NDC: 85959-003 | Form: CREAM
Manufacturer: Guangzhou Bixiaoyu Trading Co., Ltd.
Category: otc | Type: HUMAN OTC DRUG LABEL
Date: 20260210

ACTIVE INGREDIENTS: CLOTRIMAZOLE 1 g/100 g
INACTIVE INGREDIENTS: AVOCADO OIL; SOPHORA FLAVESCENS ROOT; WATER; PEPPERMINT OIL; ETHYLPARABEN; PROPYLENE GLYCOL; MELALEUCA ALTERNIFOLIA (TEA TREE) LEAF OIL; GLYCERIN; DIMETHICONE; CNIDIUM MONNIERI FRUIT

85959-003-01Kerova Clotrimazole Cream USP,1%

ACTIVE INGREDIENT

Clotrimazole 1%Antifungal

USES
· Cures most athlete's foot (tinea pedis), ringworm(tinea corporis) and jock itch (tinea cruris)· Relieves itching, burning and scaling

Keep out of reach of children. If swallowed, getmedical help or contact a Poison Control Center right away.

WARNINGS

WARNINGSFor external use only.

INDICATIONS AND USAGE

Clean the affected area and dry thoroughly.
Apply a thin layer of the product over affected area twicedaily (morning and night) or as directed by a doctor.Supervise children in the use of this product.
For athlete's foot: Pay special attention to spacesbetween the toes; wear well-fitting, ventilated shoes,and change shoes and socks at least once daily.

DOSAGE AND ADMINISTRATION

For athlete's foot and ringworm, use daily for 4 weeks.
For jock itch, use daily for 2 weeks.
If condition persists longer, consult a doctor.
This product is not effective on the scalp or nails.

INACTIVE INGREDIENT

INACTIVE INGREDIENTSWater, Peppermint Oil, Glycerin, Propylene Glycol,Ethylparaben, Dimethicone, Avocado Oil, Cnidium monnieriFruit Extract, Melaleuca alternifolia (Tea Tree) Leaf Oil,Sophora flavescens Root Extract